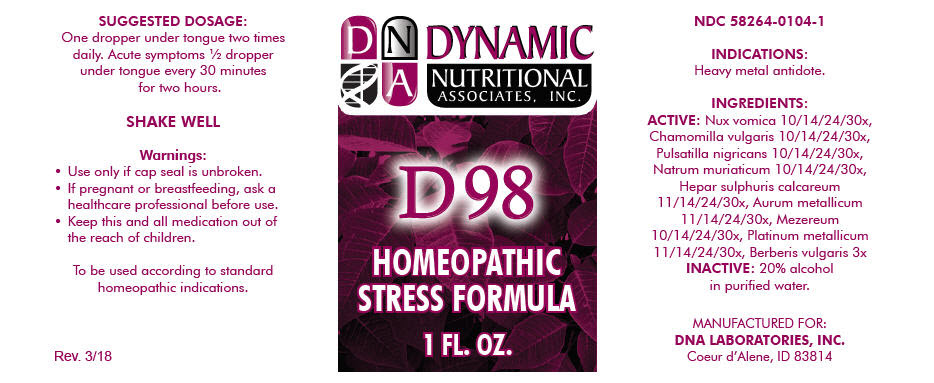 DRUG LABEL: D-98
NDC: 58264-0104 | Form: SOLUTION
Manufacturer: DNA Labs, Inc.
Category: homeopathic | Type: HUMAN OTC DRUG LABEL
Date: 20250113

ACTIVE INGREDIENTS: STRYCHNOS NUX-VOMICA SEED 10 [hp_X]/1 mL; MATRICARIA CHAMOMILLA 10 [hp_X]/1 mL; ANEMONE PRATENSIS 10 [hp_X]/1 mL; SODIUM CHLORIDE 10 [hp_X]/1 mL; CALCIUM SULFIDE 11 [hp_X]/1 mL; GOLD 11 [hp_X]/1 mL; DAPHNE MEZEREUM BARK 10 [hp_X]/1 mL; PLATINUM 11 [hp_X]/1 mL; BERBERIS VULGARIS ROOT BARK 3 [hp_X]/1 mL
INACTIVE INGREDIENTS: ALCOHOL; WATER

D-98

NDC 58264-0104-1

INDICATIONS

PURPOSE

Heavy metal antidote.

INGREDIENTS

ACTIVE

Nux vomica 10/14/24/30x, Chamomilla vulgaris 10/14/24/30x, Pulsatilla nigricans 10/14/24/30x, Natrum muriaticum 10/14/24/30x, Hepar sulphuris calcareum 11/14/24/30x, Aurum metallicum 11/14/24/30x, Mezereum 10/14/24/30x, Platinum metallicum 11/14/24/30x, Berberis vulgaris 3x

INACTIVE

20% alcohol in purified water.

SUGGESTED DOSAGE

One dropper under tongue two times daily. Acute symptoms ½ dropper under tongue every 30 minutes for two hours.

STORAGE AND HANDLING

SHAKE WELL

Warnings

- Use only if cap seal is unbroken.

PREGNANCY OR BREAST FEEDING

- If pregnant or breastfeeding, ask a healthcare professional before use.

KEEP OUT OF REACH OF CHILDREN

- Keep this and all medication out of the reach of children.

To be used according to standard homeopathic indications.

PRINCIPAL DISPLAY PANEL - 1 FL. OZ. Bottle Label

DYNAMIC
NUTRITIONAL
ASSOCIATES, INC.

D 98

HOMEOPATHIC
STRESS FORMULA

1 FL. OZ.